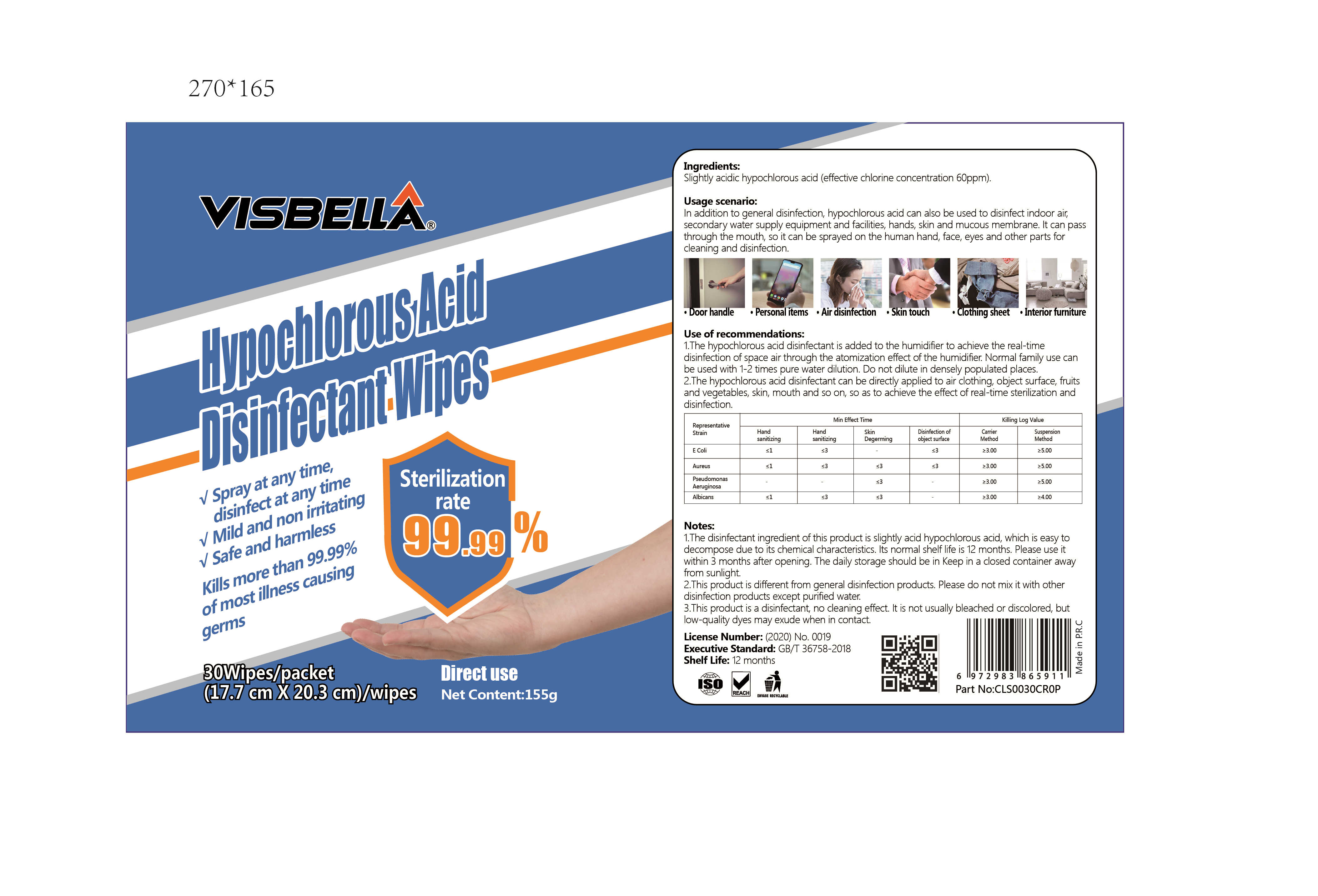 DRUG LABEL: Hypochlorous  acid disinfectant wipes
NDC: 40760-008 | Form: CLOTH
Manufacturer: Huzhou Guoneng New Material Co., Ltd.
Category: otc | Type: HUMAN OTC DRUG LABEL
Date: 20200601

ACTIVE INGREDIENTS: HYPOCHLOROUS ACID 0.93 g/30 1
INACTIVE INGREDIENTS: WATER

DOSAGE AND ADMINISTRATION

The daily storage should be in Keep in a closed container away from sunlight.

INACTIVE INGREDIENT

water

INDICATIONS AND USAGE

Open the cover and follow the form on the package

ACTIVE INGREDIENT

Hypochlorous acid

keep out of reach of children

PURPOSE

Disinfection
Sterilization

WARNINGS

1.The disinfectant ingredient of this product is slightly acid hypochlorous acid, which is easy to decompose due to its chemical characteristics. lts normal shelf life is 12months. Please use it within 3 months after opening. The daily storage should be in Keep in a closed container away from sunlight.
2.This product is dfferent from general disinfection products. Please do not mix it with other disinfection products except purifed water.
3.This product is a disinfectant, no cleaning effect. It is not usually bleached or discolored, but low-quality dyes may exude when in contact.